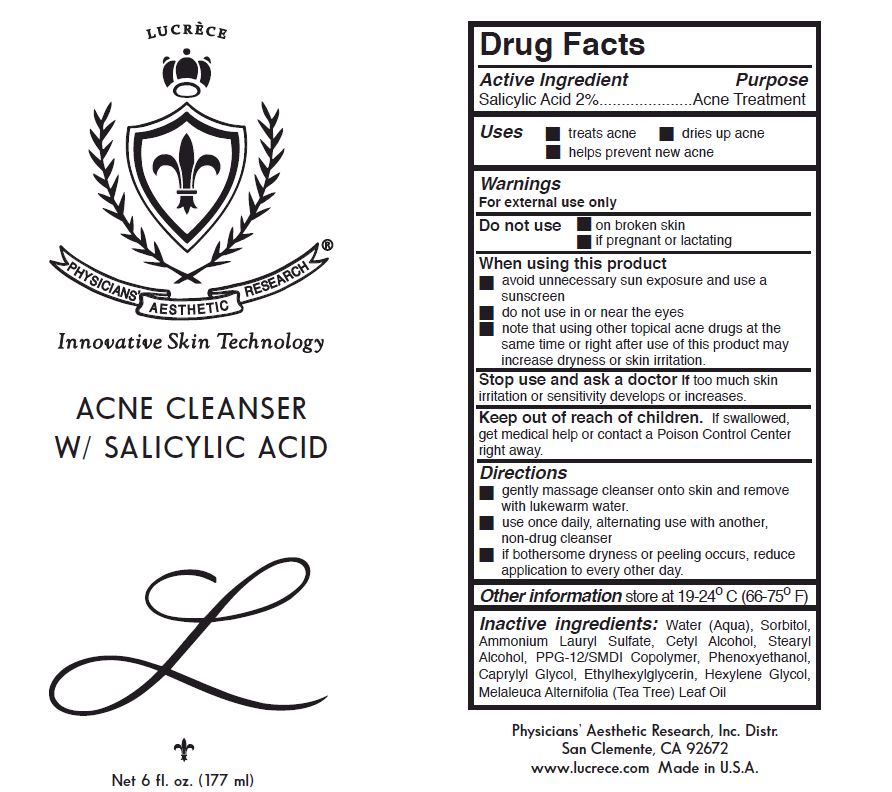 DRUG LABEL: Acne Cleanser W/ Salicylic Acid
NDC: 62742-4107 | Form: CREAM
Manufacturer: Allure Labs, Inc
Category: otc | Type: HUMAN OTC DRUG LABEL
Date: 20171201

ACTIVE INGREDIENTS: SALICYLIC ACID 20 mg/1 mL
INACTIVE INGREDIENTS: WATER; SORBITOL; AMMONIUM LAURYL SULFATE; CETYL ALCOHOL; STEARYL ALCOHOL; PPG-12/SMDI COPOLYMER; PHENOXYETHANOL; CAPRYLYL GLYCOL; ETHYLHEXYLGLYCERIN; HEXYLENE GLYCOL; MELALEUCA ALTERNIFOLIA LEAF

Drug Facts

Active Ingredient: Salicylic Acid 2%

PURPOSE

Acne Treatment

INDICATIONS AND USAGE

Uses: Treats acne

dries up acne

help prevent new acne

WARNINGS

For external use only.

Do not use :

on the broken skin

if pregnant or lactating

WHEN USING

avoid unnecessary sun exposure and use a sunscreen.

do not use in or near the eyes.

not that using other topical acne drugs at the same time or right after use of this product may increase dryness or skin irritation.

STOP USE

Stop useand ask a doctor if too much skin irritation or sensitivity develops or increase.

KEEP OUT OF REACH OF CHILDREN

if swallowed, get medical help or contact a Poison Control Center right away.

DOSAGE AND ADMINISTRATION

gently massage cleanser onto skin and remove with lukewarm water.

use once daily, alternating use with another, non drug cleanser.

if bothersome dryness or peeling occurs, reduce application to every other day.

OTHER SAFETY INFORMATION

store at 19-24 C (66-75 F)

INACTIVE INGREDIENT

Inactive Ingredients: Water (Aqua), Sorbitol, Ammonium Lauryl Sulfate, Cetyl Alcohol, Stearyl Alcohol, PPG-12/SMDI Copolymer, Phenoxyethanol, CAprylyl Glycol, Ethylhexylglycerin, Hexylene Glycol, Melaleuca Alternifolia (Tea Tree) Leaf Oil.

PACKAGE LABEL

Physician's Aesthetic Research, Inc Distr.

San Clemente, CA 92672

www.lucrece.com

Made in USA